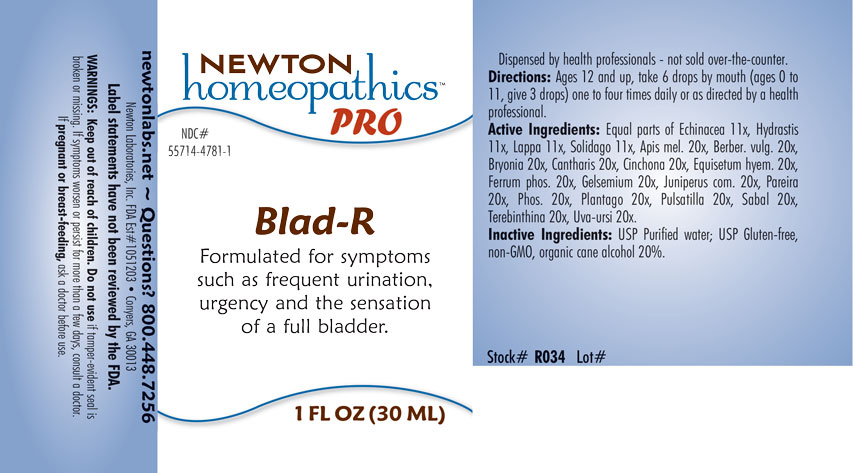 DRUG LABEL: Blad-R
NDC: 55714-4781 | Form: LIQUID
Manufacturer: Newton Laboratories, Inc.
Category: homeopathic | Type: HUMAN OTC DRUG LABEL
Date: 20201202

ACTIVE INGREDIENTS: APIS MELLIFERA 20 [hp_X]/1 mL; BERBERIS VULGARIS ROOT BARK 20 [hp_X]/1 mL; BRYONIA ALBA ROOT 20 [hp_X]/1 mL; LYTTA VESICATORIA 20 [hp_X]/1 mL; CINCHONA OFFICINALIS BARK 20 [hp_X]/1 mL; EQUISETUM HYEMALE 20 [hp_X]/1 mL; FERROSOFERRIC PHOSPHATE 20 [hp_X]/1 mL; GELSEMIUM SEMPERVIRENS ROOT 20 [hp_X]/1 mL; JUNIPER BERRY 20 [hp_X]/1 mL; CHONDRODENDRON TOMENTOSUM ROOT 20 [hp_X]/1 mL; PHOSPHORUS 20 [hp_X]/1 mL; PLANTAGO MAJOR 20 [hp_X]/1 mL; ANEMONE PULSATILLA 20 [hp_X]/1 mL; SAW PALMETTO 20 [hp_X]/1 mL; TURPENTINE OIL 20 [hp_X]/1 mL; ARCTOSTAPHYLOS UVA-URSI LEAF 20 [hp_X]/1 mL; ECHINACEA, UNSPECIFIED 11 [hp_X]/1 mL; GOLDENSEAL 11 [hp_X]/1 mL; ARCTIUM LAPPA ROOT 11 [hp_X]/1 mL; SOLIDAGO VIRGAUREA FLOWERING TOP 11 [hp_X]/1 mL
INACTIVE INGREDIENTS: ALCOHOL; WATER

Blad-R 4781L

INDICATIONS & USAGE SECTION

Formulated for symptoms such as frequent urination, urgency and the sensation of a full bladder.

DOSAGE & ADMINISTRATION SECTION

Directions: Ages 12 and up, take 6 drops by mouth (ages 0 to 11, give 3 drops) one to four times daily or as directed by a health professional.

OTC - ACTIVE INGREDIENT SECTION

Equal parts of Echinacea 11x, Hydrastis 11x, Lappa 11x, Solidago 11x., Apis mel. 20x, Berber. vulg. 20x, Bryonia 20x, Cantharis 20x, Cinchona 20x, Equisetum hyemale 20x, Ferrum phos.20x, Gelsemium 20x, Juniperus com. 20x, Pareira 20x, Phos. 20x, Plantago 20x, Pulsatilla 20x, Sabal 20x, Terebinthina 20x, Uva-ursi 20x.

OTC - PURPOSE SECTION

Formulated for symptoms such as frequent urination, urgency and the sensation of a full bladder.

INACTIVE INGREDIENT SECTION

Inactive Ingredients: USP Purified Water; USP Gluten-free, non-GMO, organic cane alcohol 20%.

QUESTIONS SECTION

newtonlabs.net – Questions? 800.448.7256

Newton Laboratories, Inc. FDA Est # 1051203 - Conyers, GA 30013

WARNINGS SECTION

WARNINGS: Keep out of reach of children. Do not use if tamper-evident seal is broken or missing. If symptoms worsen or persist for more than a few days, consult a doctor. If pregnant or breast-feeding, ask a doctor before use.

OTC - PREGNANCY OR BREAST FEEDING SECTION

If pregnant or breast-feeding, ask a doctor before use.

OTC - KEEP OUT OF REACH OF CHILDREN SECTION

Keep out of reach of children